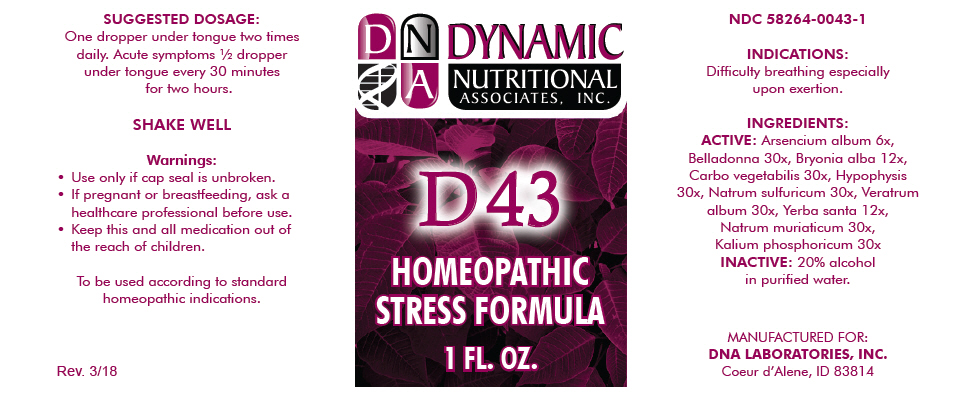 DRUG LABEL: D-43
NDC: 58264-0043 | Form: SOLUTION
Manufacturer: DNA Labs, Inc.
Category: homeopathic | Type: HUMAN OTC DRUG LABEL
Date: 20250113

ACTIVE INGREDIENTS: ARSENIC TRIOXIDE 6 [hp_X]/1 mL; ATROPA BELLADONNA 30 [hp_X]/1 mL; BRYONIA ALBA ROOT 12 [hp_X]/1 mL; ACTIVATED CHARCOAL 30 [hp_X]/1 mL; BOS TAURUS PITUITARY GLAND, POSTERIOR 30 [hp_X]/1 mL; SODIUM SULFATE 30 [hp_X]/1 mL; VERATRUM ALBUM ROOT 30 [hp_X]/1 mL; ERIODICTYON CALIFORNICUM LEAF 12 [hp_X]/1 mL; SODIUM CHLORIDE 30 [hp_X]/1 mL; DIBASIC POTASSIUM PHOSPHATE 30 [hp_X]/1 mL
INACTIVE INGREDIENTS: ALCOHOL; WATER

D-43

NDC 58264-0043-1

INDICATIONS

PURPOSE

Difficulty breathing especially upon exertion.

INGREDIENTS

ACTIVE

Arsencium album 6x, Belladonna 30x, Bryonia alba 12x, Carbo vegetabilis 30x, Hypophysis 30x, Natrum sulfuricum 30x, Veratrum album 30x, Yerba santa 12x, Natrum muriaticum 30x, Kalium phosphoricum 30x

INACTIVE

20% alcohol in purified water.

SUGGESTED DOSAGE

One dropper under tongue two times daily. Acute symptoms ½ dropper under tongue every 30 minutes for two hours.

STORAGE AND HANDLING

SHAKE WELL

Warnings

- Use only if cap seal is unbroken.

PREGNANCY OR BREAST FEEDING

- If pregnant or breastfeeding, ask a healthcare professional before use.

KEEP OUT OF REACH OF CHILDREN

- Keep this and all medication out of the reach of children.

To be used according to standard homeopathic indications.

PRINCIPAL DISPLAY PANEL - 1 FL. OZ. Bottle Label

DYNAMIC
NUTRITIONAL
ASSOCIATES, INC.

D 43

HOMEOPATHIC
STRESS FORMULA

1 FL. OZ.